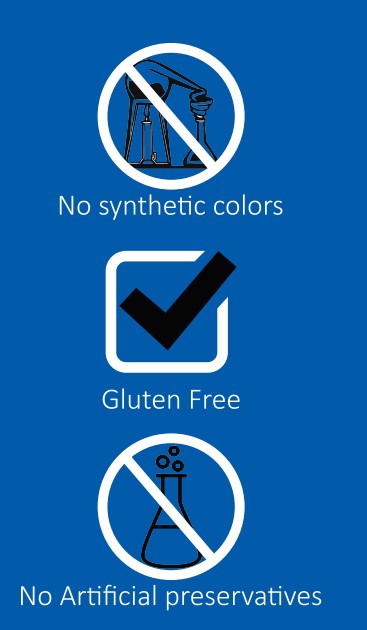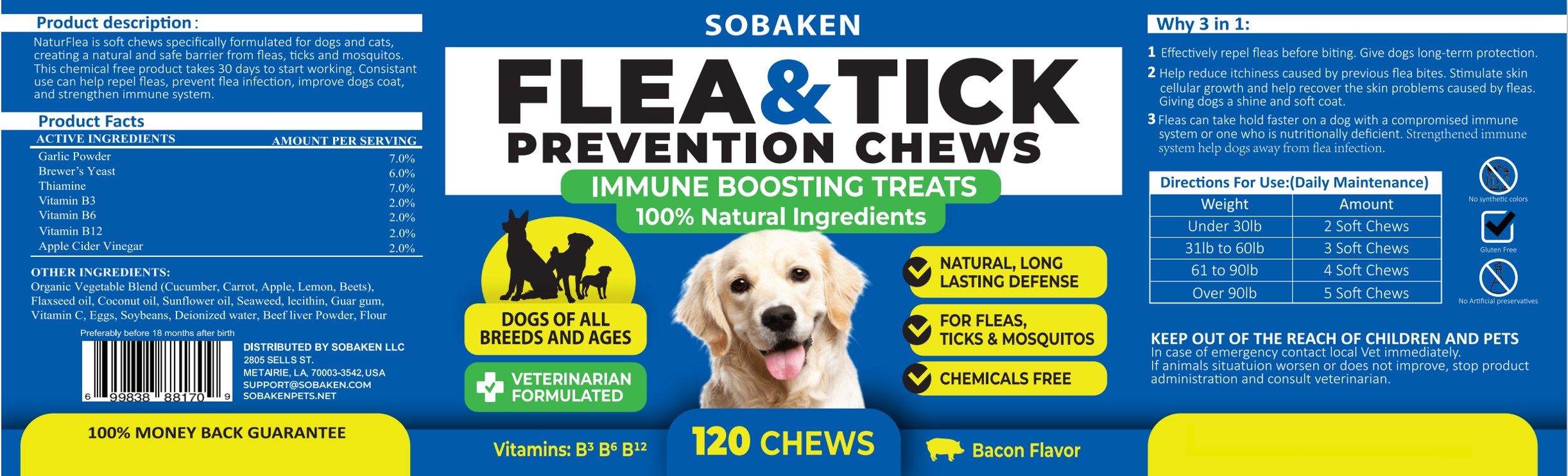 DRUG LABEL: Flea and Tick Prevention Chews
NDC: 86181-002 | Form: TABLET, CHEWABLE
Manufacturer: SOBAKEN LLC
Category: animal | Type: OTC ANIMAL DRUG LABEL
Date: 20231106

ACTIVE INGREDIENTS: GARLIC 210 mg/1 1; YEAST 180 mg/1 1; THIAMINE 210 mg/1 1; NIACIN 60 mg/1 1; PYRIDOXINE 60 mg/1 1; COBALAMIN 60 mg/1 1; APPLE CIDER VINEGAR 60 mg/1 1
INACTIVE INGREDIENTS: CUCUMBER 10 mg/1 1; CARROT 10 mg/1 1; APPLE 10 mg/1 1; LEMON 10 mg/1 1; BEET 10 mg/1 1; LINSEED OIL 10 mg/1 1; COCONUT OIL 10 mg/1 1; SUNFLOWER OIL 10 mg/1 1; NORI 10 mg/1 1; LECITHIN, SOYBEAN 10 mg/1 1; EGG 10 mg/1 1; SOYBEAN 10 mg/1 1; WATER 10 mg/1 1; BEEF LIVER 10 mg/1 1; WHEAT 10 mg/1 1; ASCORBIC ACID 10 mg/1 1; GUAR GUM 10 mg/1 1

Flea&tick Prevention Chews

Directions For Use:(Daily Maintenance)

Weight Amount
Under 30lb.............2 Soft Chews
31lb to 60lb............3 Soft Chews
61 to 90lb..............4 Soft Chews
Over 90lb...............5 Soft Chews

Cautions

KEEP OUT OF THE REACH OF CHILDREN AND PETS In case of emergency contact local Vet immediately.If animals situatuion worsen or does not improve, stop productadministration and consult veterinarian.

Why 3 in 1

1 Effectively repel fleas before biting. Give dogs long-term protection. 2 Help reduce itchiness caused by previous flea bites. Stimulate skincellular growth and help recover the skin problems caused by fleasGiving dogs a shine and soft coat. 3 Fleas can take hold faster on a dog with a compromised immunesystem or one who is nutritionally deficient. Strengthened immunesystem help dogs away from flea infection.

No synthetic colors

Gluten free

No Artificial preservatives

FRONT PANEL

FRONT PANEL SOBAKEN FLEA&TICK PREVENTION CHEWS IMMUNE BOOSTING TREATS 100% Natural Ingredients DOGS OF ALL BREEDS AND AGES VETERINARIAN FORMULATED Vitamins: B3 B6 B12 NATURAL, LONG LASTING DEFENSE
FOR FLEAS, TICKS & MOSQUITOS
CHEMICALS FREE Bacon Flavor

product description

NaturFlea is soft chews specifically formulated for dogs and cats creating a natural and safe barrier from fleas, ticks and mosquitos. This chemical free product takes 30 days to start working. Consistant use can help repel fleas, prevent flea infection, improve dogs coat, and strengthen immune system.

Active ingredient

ingredient..............amount per serving Garlic Powder.........7.0%
Brewer's Yeast........6.0%
Thiamine................7.0%
Vitamin B3.............2.0%
Vitamin B6.............2.0%
Vitamin B12............2.0%
Apple Cider Vinegar..2.0%

OTHER INGREDIENTS

Organic Vegetable Blend (Cucumber, Carrot, Apple, Lemon, Beets),Flaxseed oil, Coconut oil, Sunflower oil, Seaweed, lecithin, Guar gum,Vitamin C, Eggs, Soybeans, Deionized water, Beef liver Powder, Flour

Preferably before 18 months after birth DISTRIBUTED BY SOBAKEN LLC2805 SELLS STMETAIRIE,LA, 70003-3542,USASUPPORTOSOBAKEN.COMSOBAKENPETS.NET
100% MONEY BACK GUARANTEE

Labeling